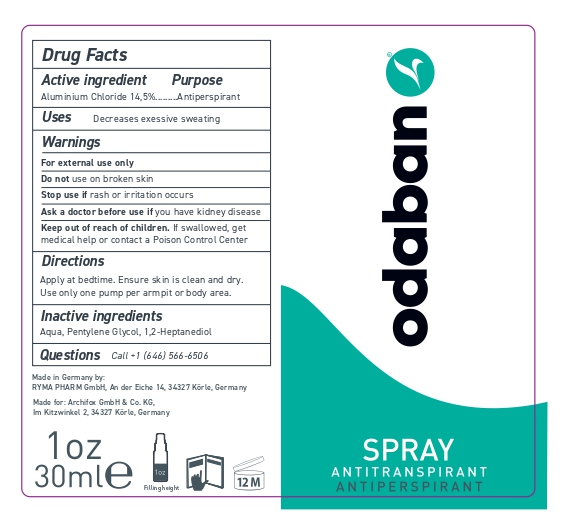 DRUG LABEL: Antiperspirant ODABAN
NDC: 84788-0001 | Form: SPRAY
Manufacturer: Ryma-Pharm GmbH
Category: otc | Type: HUMAN OTC DRUG LABEL
Date: 20251215

ACTIVE INGREDIENTS: ALUMINUM CHLORIDE 4.35 mg/30 mL
INACTIVE INGREDIENTS: AQUA REGIA; PENTYLENE GLYCOL; (6R)-2-METHYL-6-((1R,3AS,4E,7AR)-OCTAHYDRO-4-((2Z)-2-((5S)-5-HYDROXY-2-METHYLENECYCLOHEXYLIDENE)ETHYLIDENE)-7A-METHYL-1H-INDEN-1-YL)-2,4-HEPTANEDIOL

DOSAGE AND ADMINISTRATION

ODABAN® Antiperspirant Spray is a safe and simple antiperspirant that protects against excessive sweating and odour. Up to 90% sweat reduction after only 3 applications. Caution: Do not spray in eyes or apply to irritated skin. Avoid contact with clothing.

WARNINGS

Warnings For external use only Do not use on broken skin Stop use if rash or irritation occurs Ask a doctor before use if you have kidney disease Keep out of reach of children. If swallowed get medical help or contact a Poison Control Center

Inactive Ingredients Aqua, Pentylene Glycol, 1,2-Heptanediol

INDICATIONS AND USAGE

Directions Apply at bedtime. Ensure skin is clean and dry. Use only one pump per armpit or body area.

Keep out of reach of children. If swallowed get medical help or contact a Poison Control Center.

PURPOSE

Uses Decreases excessive sweating

Active Ingredient Aluminium Chloride 14,5%

PACKAGE LABEL

Drug Facts Active Ingredient Aluminium Chloride 14,5% ODABAN® Antiperspirant Spray is a safe and simple antiperspirant that protects against excessive sweating and odour. Up to 90% sweat reduction after only 3 applications. Caution: Do not spray in eyes or apply to irritated skin. Avoid contact with clothing. Made in Germany by: RYMA PHARM GmbH, An der Eiche 14, 34327 Körle, Germany Made for: Archifox GmbH & Co. KG, Im Kitzwinkel 2, 34327 Körle, Germany Filling height Inactive Ingredients Aqua, Pentylene Glycol, 1,2-Heptanediol Purpose Antiperspirant Questions Call +1 (646) 566-6506 Directions Apply at bedtime. Ensure skin is clean and dry. Use only one pump per armpit or body area. Uses Decreases excessive sweating Warnings For external use only Do not use on broken skin Stop use if rash or irritation occurs Ask a doctor before use if you have kidney disease Keep out of reach of children. If swallowed get medical help or contact a Poison Control Center.